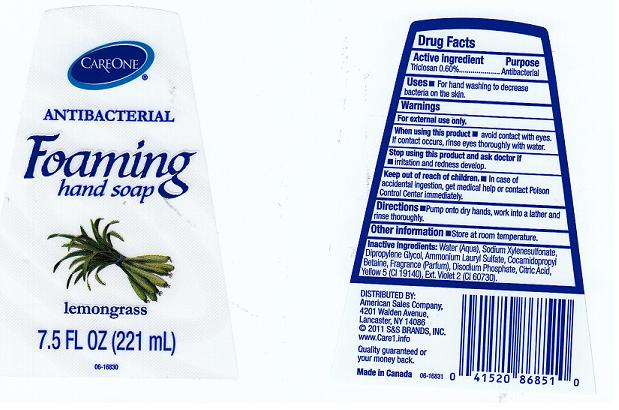 DRUG LABEL: ANTIBACTERIAL FOAMING HAND SP LEMONGRASS
NDC: 41520-172 | Form: LIQUID
Manufacturer: AMERICAN SALES
Category: otc | Type: HUMAN OTC DRUG LABEL
Date: 20110524

ACTIVE INGREDIENTS: TRICLOSAN 0.60 mL/100 mL
INACTIVE INGREDIENTS: WATER; SODIUM XYLENESULFONATE; DIPROPYLENE GLYCOL; AMMONIUM LAURYL SULFATE; COCAMIDOPROPYL BETAINE; SODIUM PHOSPHATE, DIBASIC, DIHYDRATE; CITRIC ACID MONOHYDRATE; FD&C YELLOW NO. 5; EXT. D&C VIOLET NO. 2

DRUG FACTS

ACTIVE INGREDIENT

TRICLOSAN 0.60 PERCENT

PURPOSE

ANTIBACTERIAL

USES

FOR HAND WASHING TO DECREASE BACTERIA ON THE SKIN.

WARNINGS

FOR EXTERNAL USE ONLY.

KEEP OUT OF REACH OF CHILDREN

IN CASE OF ACCIDENTAL INGESTION, GET MEDICAL HELP OR CONTACT A POISON CONTROL CENTER IMMEDIATELY.

WHEN USING THIS PRODUCT

AVOID CONTACT WITH EYES.IF CONTACT OCCURS, RINSE EYES THOROUGHLY WITH WATER.

STOP USING THIS PRODUCT AND ASK DOCTOR IF

IRRITATION AND REDNESS DEVELOP.

DIRECTIONS

PUMP ONTO DRY HANDS, WORK INTO A LATHER AND RINSE THOROUGHLY.

OTHER INFORMATION

STORE AT ROOM TEMPERATURE.

INACTIVE INGREDIENTS

Enter section text here